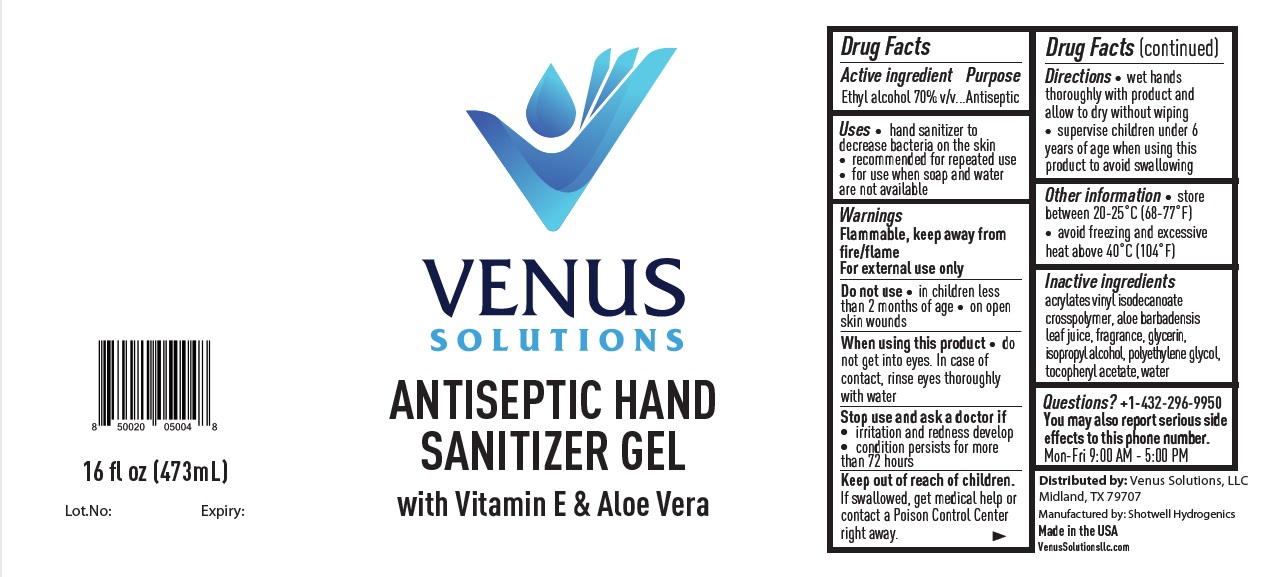 DRUG LABEL: VENUS SOLUTIONS ANTISEPTIC HAND SANITIZER
NDC: 77963-003 | Form: GEL
Manufacturer: Venus Oilfield Solutions LLC
Category: otc | Type: HUMAN OTC DRUG LABEL
Date: 20200717

ACTIVE INGREDIENTS: ALCOHOL 70 mL/100 mL
INACTIVE INGREDIENTS: ACRYLATES/VINYL ISODECANOATE CROSSPOLYMER (10000 MPA.S NEUTRALIZED AT 0.5%); ALOE VERA LEAF; GLYCERIN; ISOPROPYL ALCOHOL; POLYETHYLENE GLYCOL, UNSPECIFIED; .ALPHA.-TOCOPHEROL ACETATE; WATER

VENUS SOLUTIONS ANTISEPTIC HAND SANITIZER GEL

Active ingredient

Ethyl alcohol 70% v/v

Purpose

Antiseptic

Uses

• hand sanitizer to decrease bacteria on the skin
• recommended for repeated use
• for use when soap and water are not available

Warnings

Flammable, keep away from fire/flame

For external use only

Do not use • in children less than 2 months of age • on open skin wounds

When using this product • do not get into eyes. In case of contact, rinse eyes thoroughly with water

Stop use and ask a doctor if • irritation and redness develop • condition persists for more than 72 hours

Keep out of reach of children. If swallowed, get medical help or contact a Poison Control Center right away.

Directions

• wet hands thoroughly with product and allow to dry without wiping
• supervise children under 6 years of age when using this product to avoid swallowing

Other information

• store between 20-25°C (68-77°F)
• avoid freezing and excessive heat above 40°C (104°F)

Inactive ingredients

acrylates vinyl isodecanoate crosspolymer, aloe barbadensis leaf juice, fragrance, glycerin, isopropyl alcohol, polyethylene glycol, tocopheryl acetate, water

Questions?

+1-432-296-9950
You may also report serious side effects to this phone number.
Mon-Fri 9:00 AM - 5:00 PM

with Vitamin E & Aloe Vera

Distributed by: Venus Solutions, LLC
Midland, TX 79707

Manufactured by: Shotwell Hydrogenics
Made in the USA

VenusSolutionsllc.com